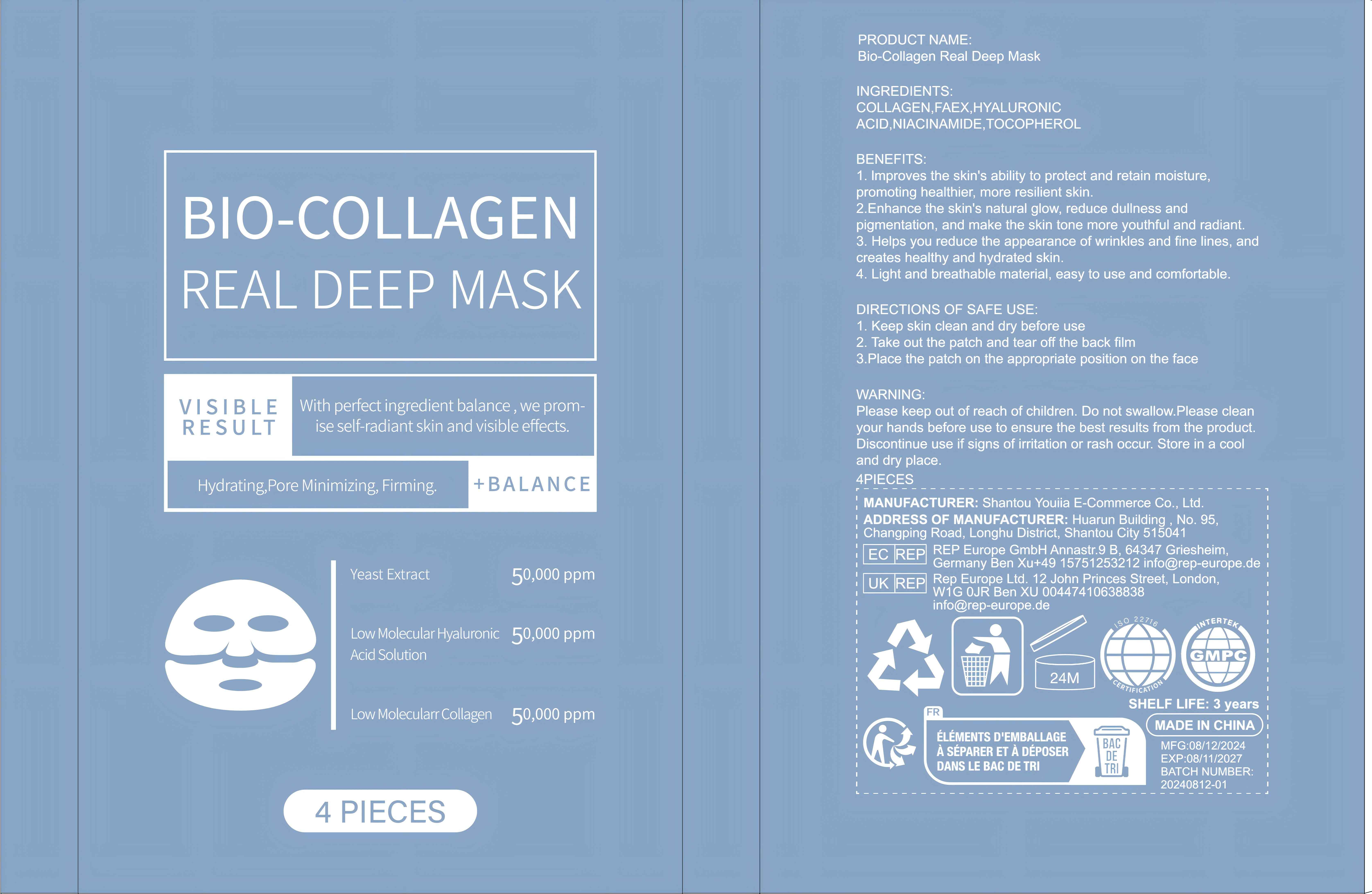 DRUG LABEL: Bio-Collagen Real Deep Mask
NDC: 84732-076 | Form: PATCH
Manufacturer: Dongguan Haiyi Technology Co.,Ltd.
Category: otc | Type: HUMAN OTC DRUG LABEL
Date: 20241030

ACTIVE INGREDIENTS: COLLAGENASE CLOSTRIDIUM HISTOLYTICUM 1 mg/100 g
INACTIVE INGREDIENTS: HYALURONIC ACID; NIACINAMIDE; TOCOPHEROL; YEAST

Active ingredient

COLLAGEN

Inactive ingredient

FAEX,HYALURONICACID,NIACINAMIDE.TOCOPHEROL

Purpose section

1. lmproves the skin's ability to protect and retain moisture,promoting healthier, more resilient skin.

2.Enhance the skin's natural glow, reduce dullness andpigmentation, and make the skin tone more youthful and radiant.

3. Helps you reduce the appearance of wrinkles and fine lines, andcreates healthy and hydrated skin.

4. Light and breathable material, easy to use and comfortable.

Warning

Please keep out of reach of children, Do not swallow.Please cleanyour hands before use to ensure the best results from the product Discontinue use if signs of irritation or rash occur. Store in a cooland dry place.

stop use

This product may cause allergic reactions in asmall number of people.
lf youexperience any discomfort,please stop using it immediately.

not use

Not suitable for use by children, pregnantor breast feeding people.

OUT OF CHILDREN

KEEP THE PRODUCT OUT OF REACH OF CHILDREN to

HOW TO USE

1. Keep skin clean and dry before use

2. Take out the patch and tear off the back film

3.Place the patch on the appropriate position on the face

Dosage

take an appropriateamount,Use 2-3 times a week